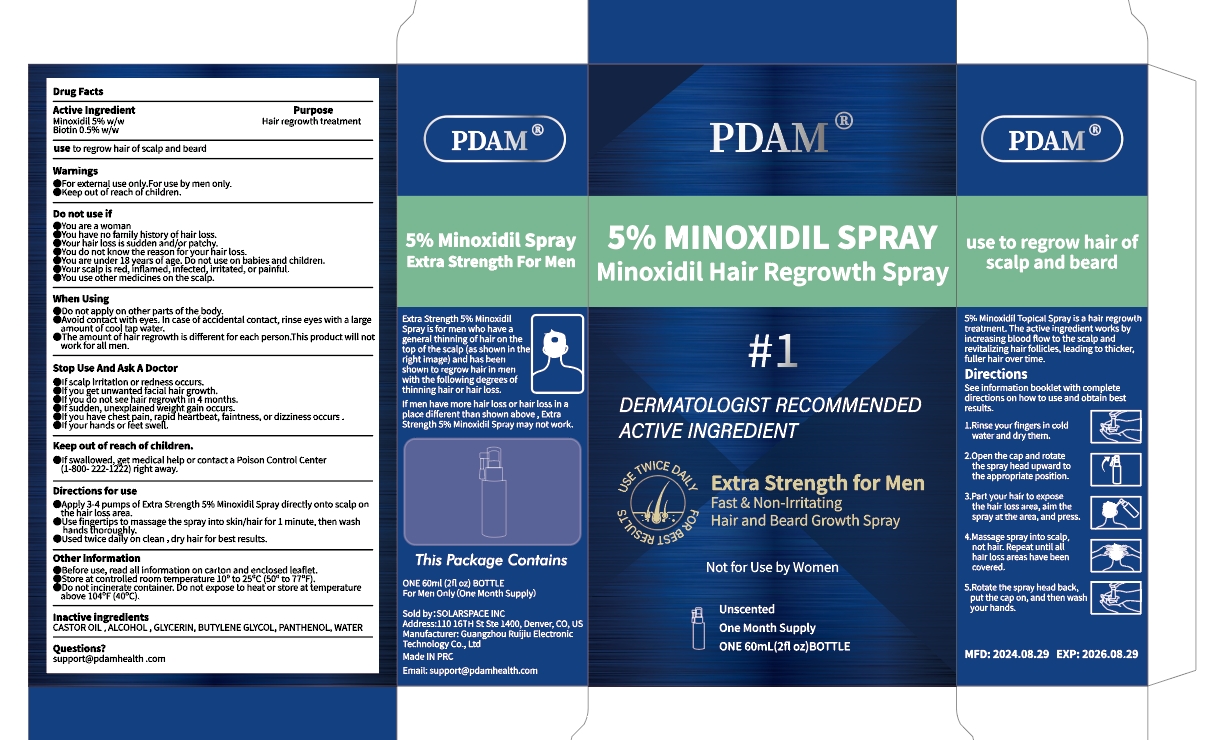 DRUG LABEL: 5% Minoxidil Hair Regrowth Sprays With Biotin
NDC: 83767-601 | Form: SPRAY
Manufacturer: Guangzhou Ruijiu Electronic Technology Co., Ltd.
Category: otc | Type: HUMAN OTC DRUG LABEL
Date: 20240903

ACTIVE INGREDIENTS: BIOTIN 0.5 g/100 mL; MINOXIDIL 5 g/100 mL
INACTIVE INGREDIENTS: WATER; ALCOHOL; CASTOR OIL; PANTHENOL; BUTYLENE GLYCOL; GLYCERIN

5% Minoxidil Hair Regrowth SPRAY With Biotin

5% Minoxidil Hair Regrowth SPRAY With Biotin

ACTIVE INGREDIENT

Minoxidil 5%
Biotin 0.5%

PURPOSE

Hair regrowth treatment

INDICATIONS AND USAGE

use to regrow hair of scalp and beard

WARNINGS

For external use only.For use by rnen only.
Keep out of reach of children.

DO NOT USE

You are a worran.
You have no family history of hair loss.
Your hair loss is sudden andjor patchy.
You do not know the reason for your hair loss.
You are under 18 years of age, Do not use on babies and children.
Your scalp is red, inflamed,infected, irritated, or painful.
You use other medicines on the scalp.

WHEN USING

Do not apply on other parts of the body.
Avoid contact with eyes, In case of accidental contact, rinse eyes with a larpe amount of cool tap water.
The amount of hair regrowth is different for each person.This product wilt hot work for all men.

STOP USE

If scalp irritation or redness occurs.
if you get unwanted facial hair growth.
if you do not see hair regrowith in 4 months.
if sudden, unexplained weight gain occurs.
if you have chest pain, rapid heartbeat, faintness, or dizziness occurs.
if your hands or feet swell.

KEEP OUT OF REACH OF CHILDREN

if swallowed, get medical help or contact a Poison Control Center(1-800-222-1222) right avray.

DOSAGE AND ADMINISTRATION

Apply 3-4 pumps of Extra Strength 5% Minoxidil Spray directly onto scalp on the hair loss area.
Use fingertips to massage the spray into skin/hair for 1 minute, then wash hands thoroughly.
Used twice daily on clean ,dry hair for best results.

STORAGE AND HANDLING

Before use, read all information on carton and enclosed leaflet.
Store at controlled room temperature 10° to 25°c (50° to 77°F).
Do not incinerate container, o not expose to heat or store at temperature above 104"F (40"C)

INACTIVE INGREDIENT

Castor oil
Alcohol
Glycerin
Butylene glycol
Panthenol
Water